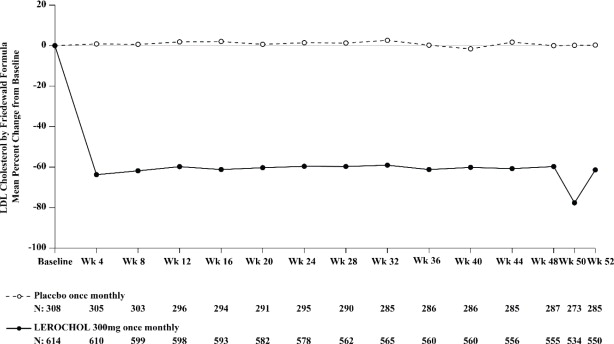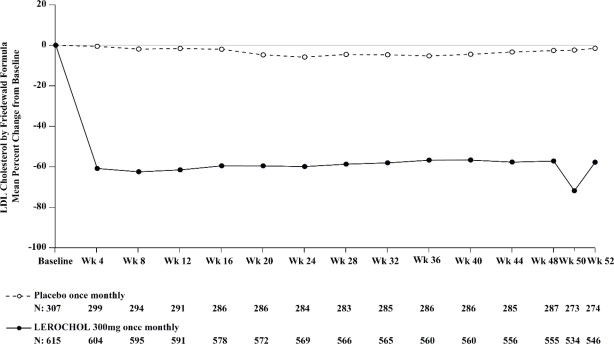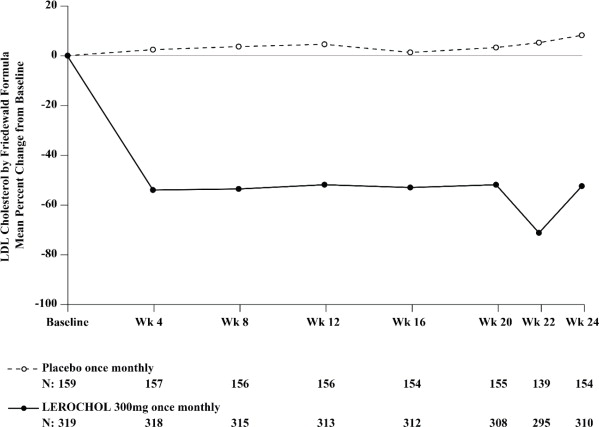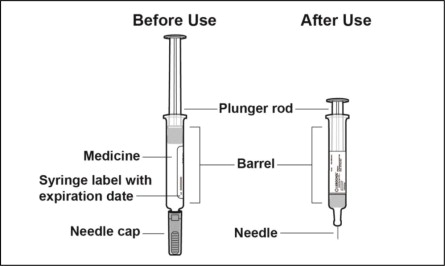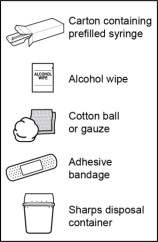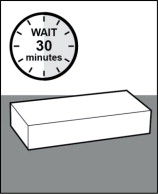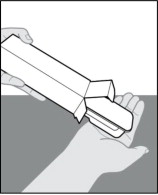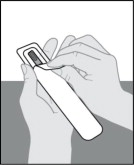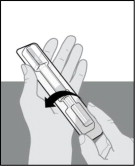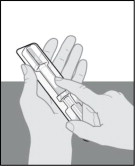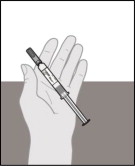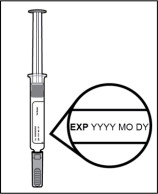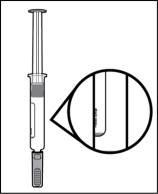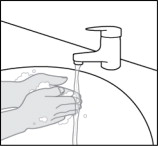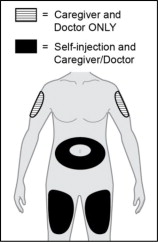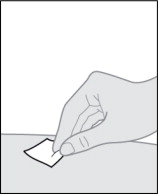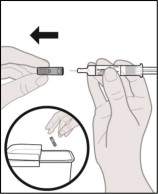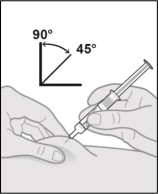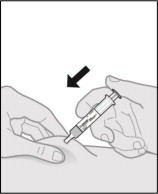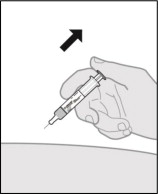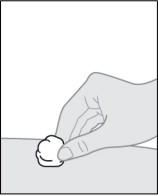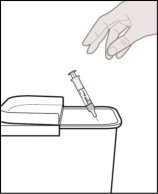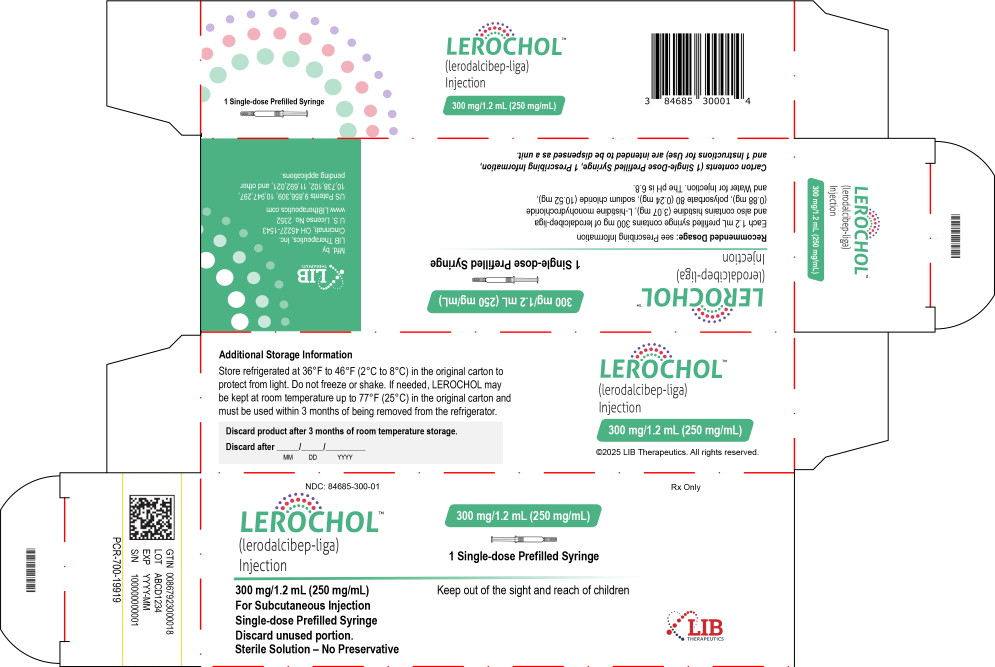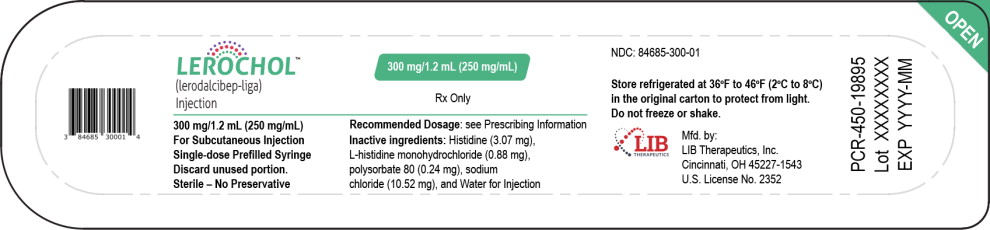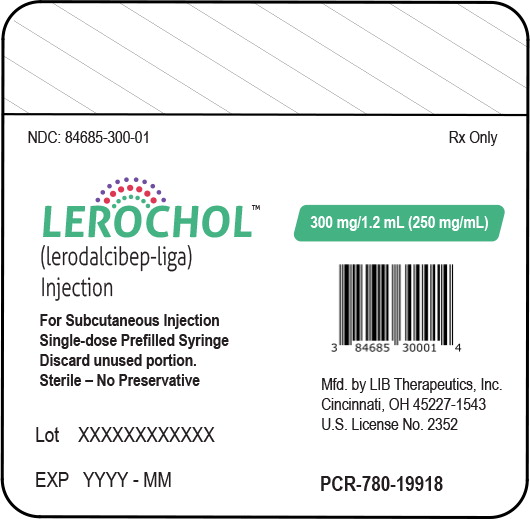 DRUG LABEL: LEROCHOL
NDC: 84685-300 | Form: INJECTION, SOLUTION
Manufacturer: LIB Therapeutics, Inc.
Category: prescription | Type: HUMAN PRESCRIPTION DRUG LABEL
Date: 20251217

ACTIVE INGREDIENTS: lerodalcibep 300 mg/1.2 mL
INACTIVE INGREDIENTS: histidine 3.07 mg/1.2 mL; histidine monohydrochloride 0.88 mg/1.2 mL; polysorbate 80 0.24 mg/1.2 mL; sodium chloride 10.52 mg/1.2 mL; Water

HIGHLIGHTS OF PRESCRIBING INFORMATION

These highlights do not include all the information needed to use LEROCHOL safely and effectively. See full prescribing information for LEROCHOL.
LEROCHOLTM (lerodalcibep-liga) injection, for subcutaneous use
Initial U.S. Approval: 2025

1 INDICATIONS AND USAGE

LEROCHOL is a proprotein convertase subtilisin kexin type 9 (PCSK9) inhibitor indicated as an adjunct to diet and exercise: to reduce low-density lipoprotein cholesterol (LDL-C) in adults with hypercholesterolemia, including heterozygous familial hypercholesterolemia (HeFH). (1)

2 DOSAGE AND ADMINISTRATION

- The recommended dosage of LEROCHOL is 300 mg administered subcutaneously once monthly. (2.1)
- Inject LEROCHOL subcutaneously into the abdomen or thigh. A caregiver or healthcare professional can administer into the upper arm. (2.2)
- Refer to the Instructions for Use for administration of prefilled syringe. (2.2)

3 DOSAGE FORMS AND STRENGTHS

Injection: 300 mg/1.2 mL (250 mg/mL) solution in a single-dose prefilled syringe. (3)

4 CONTRAINDICATIONS

None. (4)

6 ADVERSE REACTIONS

Common adverse reactions occurring in ≥1% of patients treated with LEROCHOL were injection site reactions, nasopharyngitis, diarrhea, nausea and peripheral edema. (6.1)

To report SUSPECTED ADVERSE REACTIONS, contact LIB Therapeutics, Inc. at 1-877-2-LEROCHOL or FDA at 1-800-FDA-1088 or www.fda.gov/medwatch.

FULL PRESCRIBING INFORMATION

1 INDICATIONS AND USAGE

LEROCHOLTM is indicated as an adjunct to diet and exercise to reduce low-density lipoprotein cholesterol (LDL-C) in adults with hypercholesterolemia, including heterozygous familial hypercholesterolemia (HeFH).

2 DOSAGE AND ADMINISTRATION

2.1 Recommended Dosage

- The recommended dosage of LEROCHOL is 300 mg once monthly administered subcutaneously.
- Assess LDL-C when clinically indicated. The LDL-lowering effect of LEROCHOL may be measured as early as 4 weeks after initiation and, provided monthly dosing is continued, anytime thereafter without regard to timing of the dose.

2.2 Recommendations Regarding Missed Dose(s)

- If a dose is missed by:
  - Less than 7 days, instruct the patient to administer LEROCHOL as soon as possible and resume the patient's original monthly dosage schedule.
  - Seven (7) or more days, instruct the patient to administer LEROCHOL as soon as possible and start a new monthly dosage schedule based on this date.

2.3 Important Administration Instructions

- Train patients and/or their caregivers on how to prepare and administer LEROCHOL, according to the Instructions for Use, and instruct them to read and follow the Instructions for Use each time they use LEROCHOL.
- Prior to use, allow LEROCHOL to warm to room temperature up to 25°C (77°F) for at least 30 minutes if LEROCHOL has been refrigerated [see How Supplied/Storage and Handling (16)].
- Visually inspect LEROCHOL prior to administration. LEROCHOL is a clear to slightly opalescent, brownish-yellow to amber solution. Do not use if the solution is cloudy or contains particles.
- Inject LEROCHOL subcutaneously into the abdomen or the upper front thighs. If injected by a healthcare professional or caregiver, the back of the upper arms can also be a site of injection [see Instructions for Use]. Do not inject in an area of the skin that is tender, bruised, red, or indurated. Rotate injection sites for each administration.
- To administer the full 300 mg dose, push plunger down until the syringe is empty before removing from the injection site.

3 DOSAGE FORMS AND STRENGTHS

Injection: 300 mg/1.2 mL (250 mg/mL) of clear to slightly opalescent, brownish-yellow to amber solution in a single-dose prefilled syringe.

4 CONTRAINDICATIONS

None.

6 ADVERSE REACTIONS

6.1 Clinical Trials Experience

Because clinical trials are conducted under widely varying conditions, adverse reaction rates observed in the clinical trials of a drug cannot be directly compared to rates in the clinical trials of another drug and may not reflect the rates observed in practice.

Adverse Reactions in Adults with Primary Hypercholesterolemia

Adverse Reactions in Two Pooled 52-week Controlled Trials

In two pooled 52-week, double-blind, randomized, placebo-controlled trials (Trials 1 and 2), 1,229 patients received 300 mg of LEROCHOL subcutaneously every 4 weeks [see Clinical Studies (14)]. The mean age was 64 years (range 25 to 90 years), 52% were 65 years of age or older, 37% female, 79% White, 18% Black or African American, 4% Asian; 7% identified as Hispanic or Latino ethnicity. At baseline, 9% of patients had a diagnosis of HeFH, 74% had established atherosclerotic cardiovascular disease (ASCVD), and 26% were at increased risk for ASCVD. Adverse reactions reported in at least 2% of LEROCHOL-treated patients and more frequently than in placebo-treated patients are shown in Table 1. Adverse reactions led to treatment discontinuation in 4% of LEROCHOL-treated patients and placebo-treated patients. The most frequent adverse reaction leading to treatment discontinuation was injection site reactions, with a higher frequency in the LEROCHOL-treated group compared to placebo-treated patients (1% vs. 0%).

Table 1: Adverse Reactions Occurring in ≥2% of LEROCHOL-treated Patients with Hypercholesterolemia and > 1% More Frequently than Placebo-treated Patients in Two Pooled 52-Week Trials (Trials 1 and 2)
Adverse Reactiona | LEROCHOL 300 mg (N=1,229) % | Placebo (N=612) %
Nasopharyngitis | 15 | 14
Injection site reactions | 12 | 5
Peripheral edema | 2 | <1
a Grouped terms composed of several similar terms

Adverse Reactions in a 24-Week Controlled Trial

In a 24-week, double-blind, randomized, placebo-controlled trial (Trial 3), 318 patients with HeFH received 300 mg of LEROCHOL subcutaneously every 4 weeks [see Clinical Studies (14)]. Adverse reactions reported in at least 2% of LEROCHOL-treated patients, and more frequently than in placebo-treated patients are shown in Table 2.

Table 2: Adverse Reactions Occurring in ≥2% LEROCHOL-treated Patients with HeFH and >1% More Frequently than Placebo-treated Patients at 24 Weeks (Trial 3)
Adverse Reaction | LEROCHOL 300 mg (N=318) % | Placebo (N=159) %
Injection site reactionsa | 18 | 3
Nasopharyngitisa | 13 | 9
Diarrhea | 3 | 1
Nausea | 2 | 0
Peripheral edemaa | 2 | <1
a Grouped terms composed of several similar terms

8 USE IN SPECIFIC POPULATIONS

8.1 Pregnancy

Risk Summary

Discontinue LEROCHOL when pregnancy is recognized. Alternatively, consider the ongoing therapeutic needs of the individual patient. LEROCHOL increases LDL-C uptake and lowers LDL-C levels in the circulation, thus decreasing cholesterol and possibly other biologically active substances derived from cholesterol; therefore, LEROCHOL may cause fetal harm when administered to pregnant patients based on the mechanism of action [see Clinical Pharmacology (12.1)]. In addition, treatment of hypercholesterolemia is not generally necessary during pregnancy. Atherosclerosis is a chronic process and the discontinuation of lipid-lowering drugs during pregnancy should have little impact on the outcome of long-term therapy of primary hypercholesterolemia for most patients.

Available data from clinical trials on LEROCHOL use in pregnant women are insufficient to evaluate for a drug-associated risk of major birth defects, miscarriage or other adverse maternal or fetal outcomes.

In animal reproduction studies, there were no adverse developmental effects observed when pregnant monkeys were administered lerodalcibep-liga subcutaneously during organogenesis and through to parturition at doses up to 100 mg/kg/week [up to 119-fold the exposure at the maximum recommended human dose (MRHD) of 300 mg every month].

The background risk of major birth defects and miscarriage for the indicated population is unknown. In the U.S. general population, the estimated background risk of major birth defects and miscarriage in clinically recognized pregnancies is 2% to 4% and 15% to 20%, respectively.

Data

Animal Data

In cynomolgus monkeys, no effects on embryo-fetal or postnatal development (up to 6 months of age) were observed when lerodalcibep-liga was dosed during organogenesis and through parturition at 30 and 100 mg/kg subcutaneously once weekly (exposures up to 119-fold the MRHD by AUC). An assessment of immune function in the infants showed no treatment-related adverse effects. Measurable lerodalcibep-liga serum concentrations were observed in the infant monkeys with infant serum concentrations approximately 2 to 7% of maternal serum concentrations on postnatal days 14, 21 and 28, indicating that lerodalcibep-liga has the potential to be transmitted from the mother to the developing fetus.

8.2 Lactation

Risk Summary

There are no data on the presence of lerodalcebip-liga in human milk, the effects on the breastfed infant, or the effects on milk production. In animal reproduction studies, lerodalcibep-liga was present in the milk of lactating monkeys (see Data). When a drug is present in animal milk, it is likely that the drug will be present in human milk. The developmental and health benefits of breastfeeding should be considered along with the mother's clinical need for LEROCHOL and any potential adverse effects on the breastfed infant from LEROCHOL or from the underlying maternal condition.

Data

Low concentrations of lerodalcibep-liga were measured in milk samples collected from monkeys on post-partum day (PPD) 7 and PPD 14, when lerodalcibep-liga was dosed during organogenesis through parturition at 30 and 100 mg/kg subcutaneously once weekly (exposures up to 119-fold the MRHD by AUC). There is no information regarding whether lerodalcibep-liga ingested with milk transfers to neonatal or infant monkey circulation.

8.4 Pediatric Use

The safety and effectiveness of LEROCHOL in pediatric patients have not been established. Clinical trials of LEROCHOL in pediatric patients with HeFH have not been conducted. Effectiveness of LEROCHOL was not demonstrated in a 24-week, randomized, open-label, active-controlled trial (NCT04034485) in 19 pediatric patients aged 10 to 17 years with homozygous familial hypercholesterolemia (HoFH).

8.5 Geriatric Use

Of the 1,631 patients treated with LEROCHOL 300 mg in clinical trials, 687 (42%) patients were 65 years of age and older, while 198 (12%) patients were 75 years of age or older. No overall differences in safety or effectiveness were observed between patients 65 years of age and older and younger adult patients.

8.6 Renal Impairment

No dose adjustment is necessary in patients with mild to moderate renal impairment [estimated glomerular filtration rate (eGFR) ≥30 to <90 mL/min] [see Clinical Pharmacology (12.3)]. LEROCHOL has not been studied in patients with severe renal impairment (eGFR < 30 mL/min) or end-stage renal disease.

8.7 Hepatic Impairment

No dose adjustment is necessary in patients with mild (total bilirubin 1.0 to 1.5 upper limit of normal or aspartate aminotransaminase > upper limit of normal) or moderate (total bilirubin 1.5 to 3.0 upper limit of normal) hepatic impairment [see Clinical Pharmacology (12.3)]. LEROCHOL has not been studied in patients with severe hepatic impairment.

11 DESCRIPTION

Lerodalcibep-liga is a recombinant fusion protein therapeutic agent comprised of a proprotein convertase subtilisin/kexin type 9 (PCSK9)-binding domain and human serum albumin (HSA). Lerodalcibep-liga is produced in genetically engineered mammalian (Chinese hamster ovary) cells as a single protein with an approximate molecular weight of 77 kDa.

LEROCHOL (lerodalcibep-liga) injection is a clear to slightly opalescent, brownish-yellow to amber, sterile, preservative-free solution for subcutaneous injection. Each single-dose prefilled syringe contains 1.2 mL of lerodalcibep-liga (300 mg), histidine (3.07 mg), L-histidine monohydrochloride (0.88), polysorbate 80 (0.24 mg), sodium chloride (10.52), and Water for Injection. The pH is 6.8.

12 CLINICAL PHARMACOLOGY

12.1 Mechanism of Action

Lerodalcibep-liga is a recombinant fusion protein that binds PCSK9 with picomolar affinity. PCSK9 binds to low-density lipoprotein receptor (LDLR) on the surface of hepatocytes to promote LDLR degradation within the liver. By inhibiting the binding of PCSK9 to LDLR, lerodalcibep-liga increases the number of LDLRs available to clear LDL-C from the blood, thereby lowering LDL-C levels. [see Clinical Pharmacology (12.3)].

12.2 Pharmacodynamics

After subcutaneous administration of 300 mg lerodalcibep-liga every month, greater than 90% suppression of PCSK9 occurs within 24 hours after dosing and is maintained throughout the dosing interval, returning toward baseline during the last 7 to 10 days of the monthly dosing period.

12.3 Pharmacokinetics

Following a single subcutaneous administration, exposure to lerodalcibep-liga increased in a dose proportional manner over the dose range 75 to 300 mg of lerodalcibep-liga.

Lerodalcibep-liga pharmacokinetics were observed at steady state in patients at the approved recommended dosage and are presented as mean (SD), unless otherwise specified. Lerodalcibep-liga maximum concentration (Cmax) is 31.4 (10.2) mcg/mL, and total systemic exposure (AUC0-tau) is 12,600 (5,190) (hrs*mcg/mL) following subcutaneous dose of lerodalcibep-liga 300 mg once every four weeks. Lerodalcibep-liga steady-state is reached following 2 to 3 doses. Lerodalcibep-liga accumulation is approximately 30% at the approved recommended dosage.

Absorption

The median (min, max) estimated subcutaneous bioavailability of lerodalcibep-liga is 83% (66%, 89%). The median (min, max) time to maximum plasma concentration (Tmax) is 6 days (2, 9 days) at steady state.

Distribution

Lerodalcibep-liga does not extensively distribute into tissues; the apparent volume of distribution is 5.3 L.

Elimination

As a protein, lerodalcibep-liga is expected to degrade to small peptides and amino acids. Clearance of free lerodalcibep-liga (CV%) is 0.36 L/day (30%) with an estimated half-life of approximately 10 days. The estimated elimination rate of lerodalcibep-liga (CV%) bound to PCSK9 is 0.47 L/day (22%) which corresponds to a half-life of approximately 1.5 days.

Specific Populations

No clinically significant differences in the pharmacokinetics of LEROCHOL were observed based on age (21 to 78 years), body weight, sex, race, mild (eGFR 60 to 89 mL/min) or moderate (eGFR 30 to 59 mL/min) renal impairment, or mild (total bilirubin 1.0 to 1.5 upper limit of normal or aspartate aminotransaminase greater than the upper limit of normal) or moderate (total bilirubin 1.5 to 3.0 upper limit of normal) hepatic impairment. The effect of severe renal impairment (eGFR less than 30 mL/min) or severe hepatic impairment on LEROCHOL pharmacokinetics is unknown.

Drug Interaction Studies

No formal clinical drug interaction studies have been performed.

12.6 Immunogenicity

The observed incidence of anti-drug antibodies (ADA) is highly dependent on the sensitivity and specificity of the assay. Differences in assay methods preclude meaningful comparisons of the incidence of ADA in the studies described below with the incidence of ADA in other studies, including those of lerodalcibep-liga or of other lerodalcibep products.

During the 52-week treatment period in Trial 1 and Trial 2, 15.1% (180/1,195) of LEROCHOL-treated patients at the recommended dosage with evaluable assessments were ADA positive, of whom 22.8% (41/180) had neutralizing antibodies (NAb). During the 24-week treatment period in Trial 3, 11.3% (36/318) of LEROCHOL-treated patients at the recommended dosage with evaluable assessments were ADA positive, of whom 55.6% (20/36) had NAb [see Clinical Studies (14)].

There was no identified clinically significant effect of ADA and NAb on the pharmacokinetics, pharmacodynamics (free PCSK9), safety, or effectiveness (LDL-C) of LEROCHOL over the treatment period of 52 weeks.

13 NONCLINICAL TOXICOLOGY

13.1 Carcinogenesis, Mutagenesis, Impairment of Fertility

Carcinogenicity studies have not been performed with lerodalcibep-liga.

The mutagenic potential of lerodalcibep-liga has not been evaluated; however, proteins are not expected to directly interact with DNA or chromosomes.

Fertility studies were not performed. However, in a chronic 6-month toxicology study in sexually mature cynomolgus monkeys, no adverse lerodalcibep-liga-related effects on surrogate markers of fertility (reproductive organ histopathology, menstrual cycling, or sperm parameters) were observed when lerodalcibep-liga was administered subcutaneously at 30 and 100 mg/kg once weekly. The highest dose tested corresponds to 138-fold the recommended human dose of 300 mg every month based on serum AUC.

14 CLINICAL STUDIES

The efficacy of LEROCHOL was evaluated in three randomized, double-blind, placebo-controlled trials that enrolled 2,017 adults with HeFH, clinical ASCVD, or increased risk for ASCVD, who were on a stable low-fat, low-cholesterol diet and maximally tolerated statin therapy and who required additional LDL-C lowering.

Primary Hypercholesterolemia

Trial 1 (NCT04797247) and Trial 2 (NCT04806893) were both multicenter, double-blind, randomized, placebo-controlled 52-week trials in which 1,844 adults with ASCVD or at increased risk for ASCVD events were randomized 2:1 to receive subcutaneous injections of either LEROCHOL 300 mg (n=1,229) or placebo (n=615) every 4 weeks. Patients were stable on a low-fat, low-cholesterol diet, maximally tolerated dose of statin with or without other oral lipid modifying therapy, and required additional LDL-C reduction.

Baseline Disease and Demographic Characteristics

The mean age in Trial 1 at baseline was 64 years (range: 25 to 90 years), 49% were 65 years or older, 30% were female, 80% were White, 17% were Black or African American, and 3% were Asian; 1.1% identified as Hispanic or Latino ethnicity. Thirty four percent (34%) of patients had diabetes at baseline, 86% established ASCVD, and 14% at increased risk for CVD events. The mean baseline LDL-C was 102 mg/dL. At the time of randomization, 87% of patients were receiving statin therapy and of these 53% were receiving high-intensity statin therapy; 18% were receiving ezetimibe either in combination with a statin or alone.

The mean age in Trial 2 at baseline was 65 years (range: 27 to 87 years), 54% were 65 years or older, 45% were female, 78% were White, 18% were Black or African American, and 4% were Asian; 13% identified as Hispanic or Latino ethnicity. Forty-three percent (43%) of patients had diabetes at baseline, 48% established ASCVD, and 52% at increased risk for CVD events. The mean baseline LDL-C was 116 mg/dL. At the time of randomization, 83% of patients were receiving statin therapy and of these, 39% were on high-intensity doses; 17% were receiving ezetimibe either in combination with a statin or alone.

Endpoint Results

The primary efficacy outcome measure in Trial 1 was the placebo adjusted intent to treat (ITT) analysis of percent change in LDL-C from baseline to Week 52. The difference between the LEROCHOL and placebo group in mean percentage change in LDL-C from baseline to Week 52 was -55% (95% CI: -59.2%, -50.8%; p < 0.0001). For additional results, see Table 3 and Figure 1.

Table 3: Changes in Lipid Parameters in Patients with Hypercholesterolemia and ASCVD or Increased Risk for ASCVD Events on Maximally Tolerated Statin Therapy (Percent Change from Baseline to Week 52 in Trial 1)
Treatment Group | LDL-Ca | Total Cholesterola | Non-HDL-Ca | ApoBa
Placebo (n = 308) | -0.1 | -0.2 | -0.7 | +1
LEROCHOL 300mg (n = 614) | -55 | -31 | -46 | -39
Difference from placebo (LS Mean) (95% CI) | -55b,c (-59, -51) | -31b,d (-33, -28) | -45b,d (-48, -41) | -40b,d (-44, -37)
Abbreviation: ApoB = apolipoprotein B; CI = confidence interval; HDL-C = high-density lipoprotein cholesterol; LDL-C = low-density lipoprotein cholesterol; n = number of patients randomly assigned to each treatment group; LS Mean= least-squares mean
a LDL-C, Total Cholesterol, non-HDL-C and ApoB at Week 52 were missing for 7.5% and 10.4% of patients assigned to placebo and LEROCHOL, respectively. Multiple imputation washout model was implemented for imputing missing values at Week 52.
b Least-squares mean from an Analysis of Covariance (ANCOVA) model including treatment as a factor and baseline value as a covariate, assuming unequal variances between groups.
c p-value <0.001 for superiority, controlled for Type I error rate.
d Not controlled for Type I error rate.

Figure 1: Mean Percent Change from Baseline in LDL-C Over 52 Weeks in Patients with Hypercholesterolemia and ASCVD or Increased Risk for ASCVD Events on Maximally Tolerated Statin Therapy (Trial 1)

The primary efficacy outcome measure in Trial 2 was the percent change in LDL-C from baseline compared to placebo to Week 52. The difference between the LEROCHOL and placebo groups by ITT analysis in mean percentage change in LDL-C from baseline to Week 52 was -50% (95% CI: -54.2%, -45.2%; p < 0.0001). For additional results, see Table 4 and Figure 2.

Table 4: Changes in Lipid Parameters in Patients with Hypercholesterolemia and ASCVD or Increased Risk for ASCVD Events on Maximally Tolerated Statin Therapy (Percent Change from Baseline to Week 52 in Trial 2)
Treatment Group | LDL-Ca | Total Cholesterola | Non-HDL-Ca | ApoBa
Placebo (n = 307) | +0.3 | +1 | +1 | +2
LEROCHOL 300mg (n = 615) | -49 | -28 | -41 | -36
Difference from placebo (LS Mean) (95% CI) l | -50b,c (-54, -45) | -29b,d (-32, -26) | -42b,d (-46, -38) | -38b,d (-42, -35)
Abbreviation: ApoB = apolipoprotein B; CI = confidence interval; HDL-C = high-density lipoprotein cholesterol; LDL-C = low-density lipoprotein cholesterol; n = number of patients randomly assigned to each treatment group; LS Mean = least-squares mean
a LDL-C and non-HDL-C at Week 52 were missing for 10.7% and 11.2% of patients assigned to placebo and LEROCHOL, respectively. Total Cholesterol and ApoB at Week 52 were missing for 10.4% and 11.2% of patients assigned to placebo and LEROCHOL, respectively. Multiple imputation washout model was implemented for imputing missing values at Week 52.
b Least-squares mean from an Analysis of Covariance (ANCOVA) model including treatment and CVD status as factors and baseline value as a covariate, assuming unequal variances between groups.
c p-value <0.001 for superiority, controlled for Type I error rate.
d Not controlled for Type I error rate.

Figure 2: Mean Percent Change from Baseline in LDL-C Over 52 Weeks in Patients with Hypercholesterolemia and ASCVD or Increased Risk for ASCVD Events on Maximally Tolerated Statin Therapy (Trial 2)

Heterozygous Familial Hypercholesterolemia in Adults

Trial 3 (NCT04797104) was a multicenter, double-blind, randomized, placebo-controlled 24-week trial in which 478 patients with HeFH were randomized 2:1 to receive subcutaneous injections of either LEROHOL 300 mg (n = 319) or placebo (n = 159) every 4 weeks. Patients were stable on diet, maximally tolerated dose of statin, with or without other oral lipid modifying therapy, and required additional LDL-C reduction.

Baseline Disease and Demographic Characteristics

The mean age at baseline was 53 years (range: 18 to 80 years), 19% were aged 65 years or older, 52% were female, 87% were White, 8% were Black or African American, and 5% were Asian; 1% identified as Hispanic or Latino ethnicity. Forty-five percent of patients had diabetes at baseline. The mean baseline LDL-C was 150 mg/dL. At the time of randomization, 89% of patients were receiving statin therapy with 67% receiving high-intensity doses, and 49% also on ezetimibe.

Endpoint Results

The primary efficacy outcome measure in Trial 3 was the percent change in LDL-C from baseline to Week 24. The difference between the LEROCHOL and placebo groups in mean percentage change in LDL-C from baseline to Week 24 was -59% (95% CI: -65.7%, -51.7%; p < 0.0001). For additional results, see Table 5 and Figure 3.

Table 5: Changes in Lipid Parameters in Patients with HeFH, on Maximally Tolerated Statin Therapy (Percent Change from Baseline to Week 24 in Trial 3)
Treatment Group | LDL-Ca | Total Cholesterola | Non-HDL-Ca | ApoBa
Placebo (n = 159) | + 8 | +5 | +7 | +7
LEROCHOL 300mg (n = 319) | -51 | -32 | -44 | -37
Difference from placebo (LS Mean) (95% CI) | -59b,c (-66, -52) | -37b,d (-41, -32) | -51b,d (-57, -45) | -44b,d (-49, -39)
Abbreviation: ApoB = apolipoprotein B; CI = confidence interval; HDL-C = high-density lipoprotein cholesterol; LDL-C = low-density lipoprotein cholesterol; n = number of patients randomly assigned to each treatment group; LS Mean = least-squares mean
a LDL-C, Total Cholesterol and non-HDL-C at Week 24 were missing for 3.1% and 2.8% of patients assigned to placebo and LEROCHOL, respectively. ApoB at Week 24 was missing for 3.1% and 3.1% of patients assigned to placebo and LEROCHOL, respectively. Multiple imputation washout model was implemented for imputing missing values at Week 24.
b Least-squares mean from an Analysis of Covariance (ANCOVA) model including treatment and CVD status as factors and baseline value as a covariate, assuming unequal variances between groups.
c p-value <0.001 for superiority, controlled for Type I error rate.
d Not controlled for Type I error rate.

Figure 3: Mean Percent Change from Baseline in LDL-C Over 24 Weeks in Patients with HeFH on Maximally Tolerated Statin Therapy (Trial 3)

16 HOW SUPPLIED/STORAGE AND HANDLING

How Supplied

LEROCHOL (lerodalcibep-liga) injection 300 mg/1.2 mL (250 mg/mL) is supplied as a single-dose prefilled syringe for subcutaneous injection and is a clear to slightly opalescent, brownish-yellow to amber, sterile, preservative-free solution.

LEROCHOL is supplied in cartons containing one single-dose prefilled syringe (NDC 84685-300-01).

Storage and Handling

Store refrigerated at 2°C to 8°C (36°F to 46°F) in the original carton to protect from light. Do not freeze. Do not shake.

If needed, LEROCHOL may be kept at room temperature up to 25°C (77°F) in the original carton and must be used within 3 months of being removed from the refrigerator. If not used within 3 months, discard LEROCHOL. Do not use beyond the expiration date on the container or package.

17 PATIENT COUNSELING INFORMATION

Advise the patient and/or caregiver to read the FDA-Approved Patient Labeling (Patient Information and Instructions for Use).

Administration

Provide guidance to patients and caregivers on proper subcutaneous injection technique and how to use the prefilled syringe correctly. Inform patients that the prefilled syringe should be allowed to warm to room temperature for 30 minutes prior to use, if refrigerated [see Dosage and Administration (2.3)].

Manufactured by: LIB Therapeutics, Inc.
5375 Medpace Way
Cincinnati, OH 45227-1543
Version 0.5

Patient Information
LEROCHOLTM (leer-O-call)
(lerodalcibep-liga)
injection, for subcutaneous use

What is LEROCHOL?
LEROCHOL is an injectable prescription medicine used along with diet and exercise to reduce low-density lipoprotein cholesterol (LDL-C) or bad cholesterol in adults with high blood cholesterol levels called hypercholesterolemia including heterozygous familial hypercholesterolemia (HeFH).
It is not known if LEROCHOL is safe and effective in children.

What should I tell my healthcare provider before using LEROCHOL?
Before you start using LEROCHOL, tell your healthcare provider about all of your medical conditions, including if you:

- are pregnant or plan to become pregnant. It is not known if LEROCHOL will harm your unborn baby. Tell your healthcare provider if you become pregnant while taking LEROCHOL.
- are breastfeeding or plan to breastfeed. You and your healthcare provider should decide if you will take LEROCHOL or breastfeed. You should not do both without talking to your healthcare provider first.

Tell your healthcare provider or pharmacist about all the medicines you take, including prescription and over-the-counter medicines, vitamins, and herbal supplements.

How should I use LEROCHOL?

- See the detailed Instructions for Use that comes with this Patient Information about the right way to prepare and give your LEROCHOL injections.
- Use LEROCHOL exactly as your healthcare provider tells you to use it.
- LEROCHOL comes as a single-dose (1 time) prefilled syringe.
- If your healthcare provider decides that you or a caregiver can give the injections of LEROCHOL, you or your caregiver should receive training on the right way to prepare and give LEROCHOL. Do not try to inject LEROCHOL until you have been shown the right way by your healthcare provider or nurse.
- LEROCHOL is injected under the skin (subcutaneously) 1 time every month.
- LEROCHOL can be self-injected in the stomach area, at least 2 inches away from the belly button or upper front of the legs (thighs).
- LEROCHOL can be injected by a caregiver or healthcare provider in the back of the upper arm.
- Do not choose an area where the skin is tender, bruised, red, or hard.
- Do not inject LEROCHOL together with other injectable medicines at the same injection site.
- Always check the label of your syringe to make sure you have the correct medicine.
- If you forget to use LEROCHOL or are not able to take the dose on your regular schedule, inject your missed dose as soon as you remember if it has been less than 7 days of the missed dose and continue the original monthly dosage schedule.
- If it is 7 or more days from the missed dose, inject the dose and start a new monthly schedule using the date LEROCHOL was taken. If you are not sure when to re-start LEROCHOL, ask your healthcare provider or pharmacist.
- If you use more LEROCHOL than you should, talk to your healthcare provider or pharmacist.
- Do not stop using LEROCHOL without talking with your healthcare provider. If you stop using LEROCHOL, your cholesterol levels can increase.

What are the possible side effects of LEROCHOL?
The common side effects of LEROCHOL include:

- redness, itching, swelling, pain, bruising or tenderness at the injection site
- runny or stuffy nose, sore throat (nasopharyngitis)
- diarrhea
- nausea
- swelling in arms, hands, legs, or feet (peripheral edema)

Tell your healthcare provider if you have any side effect that bothers you or that does not go away. Ask your healthcare provider or pharmacist for more information.
Call your doctor for medical advice about side effects. You may report side effects to FDA at 1-800- FDA-1088.

How should I store LEROCHOL?

- Store LEROCHOL in the refrigerator between 36°F to 46°F (2°C to 8°C) in the original carton until ready to use and to protect from light.
- If needed, LEROCHOL may be kept at room temperature between 68°F to 77°F (20°C to 25°C) in the original carton for up to 3 months after being removed from the refrigerator. Throw away LEROCHOL that has been stored at room temperature for more than 3 months.
- Do not freeze.
- Do not shake.

Keep LEROCHOL and all medicines out of reach of children.

General information about the safe and effective use of LEROCHOL.
Medicines are sometimes prescribed for purposes other than those listed in a Patient Information leaflet. Do not use LEROCHOL for a condition for which it was not prescribed. Do not give LEROCHOL to other people, even if they have the same symptoms that you have. It may harm them.
You can ask your pharmacist or healthcare provider for information about LEROCHOL that is written for health professionals.

What are the ingredients in LEROCHOL?

- Active ingredient: lerodalcibep-liga
- Inactive ingredients: histidine, L-histidine monohydrochloride, polysorbate 80, sodium chloride, and Water for Injection, USP.

Manufactured by: LIB Therapeutics, Inc. 5375 Medpace Way, Cincinnati, OH 45227-1543, U.S. License # 2352; LEROCHOL is a registered trademark of LIB Therapeutics, Inc. / ©2024 LIB Therapeutics, Inc. All rights reserved.
Version 0.3
For more information about LEROCHOL, go to www.LEROCHOL.com or call 1-877-2-LEROCHOL (1-877-253-7624).

This Patient Package Insert has been approved by the U.S. Food and Drug Administration.

12/2025

INSTRUCTIONS FOR USE

LEROCHOLTM [leer-O-call]

(lerodalcibep-liga)

injection, for subcutaneous use only

Single-dose Prefilled Syringe

This Instructions for Use contains information on how to inject LEROCHOL.

Read and follow these instructions before you start using the LEROCHOL prefilled syringe and each time you get a refill. There may be new information. This information does not take the place of talking with your healthcare provider about your medical condition or your treatment.

Do not use the LEROCHOL prefilled syringe until your healthcare provider has given you instructions on the right way to give an injection.

Parts of the Prefilled Syringe (see Figure A)

Figure A

Important Information You Need to Know Before Injecting LEROCHOL

- For subcutaneous injection only (inject under the skin).
- Do not use LEROCHOL if the seals on the sides of the carton have already been broken. If seals have already been broken, LEROCHOL may have been tampered with, get a new carton.
- Do not use LEROCHOL if the prefilled syringe is dropped or damaged. Get a new carton.
- Do not re-cap the prefilled syringe as you may stick yourself or damage the needle.
- Do not freeze.
- Safely throw away (dispose of) the used prefilled syringe after the injection is completed (see Step 15. Dispose of used prefilled syringe).

Preparing to Inject LEROCHOL

Step 1. Gather the supplies needed to give the injection.

1. Choose a clean, flat surface in a well-lit area.
2. Gather the following supplies and place them on the surface (see Figure B):
  - Carton containing prefilled syringe
    Items not included in the carton:
    - Alcohol wipe
    - Cotton ball or gauze
    - Adhesive bandage
    - FDA-cleared Sharps disposal container

Figure B

Step 2. If refrigerated, let the prefilled syringe warm to room temperature for 30 minutes.

1. Let the carton sit at room temperature for 30 minutes before use (see Figure C).
2. Keep the prefilled syringe in the carton during warm-up to protect from light.
  - Letting the prefilled syringe warm to room temperature will make the injection more comfortable.
  - Do not use a heat source such as a microwave or warm the carton containing the prefilled syringe any other way.
  - Do not shake the carton.

Figure C

Step 3. Remove the plastic tray from the carton.

1. Break the seal and open the side of the carton.
  - Do not use LEROCHOL if the seals on the sides of the carton have already been broken. If seals have already been broken, LEROCHOL may have been tampered with, get a new carton.
2. Gently slide the plastic tray containing the prefilled syringe from the carton into the palm of your hand (Figure D).

Figure D

Step 4. Remove the prefilled syringe from the plastic tray.

1. Place the plastic tray on your hand and peel off the paper seal with your other hand (see Figure E).
2. Turn the plastic tray over and gently press the middle of the tray's back to release the prefilled syringe into the palm of your hand (see Figures F, G and H).

Figure E

Figure F

Figure G

Figure H

- Do not pick up or pull the prefilled syringe by the plunger rod or gray needle cap. This could damage the syringe.
- Do not remove the gray needle cap from the prefilled syringe until you are ready to inject.
- Always hold the prefilled syringe by the syringe barrel.

Step 5. Inspect the prefilled syringe.

1. Make sure LEROCHOL appears on the prefilled syringe label.
2. Check the expiration (EXP) date (see Figure I).
3. Check the prefilled syringe for damage.
  - Do not use and get a new carton if LEROCHOL does not appear on the label, the expiration date has passed, or there are signs of damage.

Figure I

Step 6. Inspect the medicine.

1. Check the medicine to make sure the liquid is clear to brownish-yellow or amber (see Figure J).
  - Do not use the prefilled syringe if the liquid is cloudy or contains visible particles. Get a new carton.

Figure J

Step 7. Wash your hands.

1. Wash your hands with soap and water and dry them thoroughly (see Figure K).

Figure K

Step 8. Choose an injection site.

1. Choose an injection site from the following areas (see Figure L):
  - Stomach area (abdomen) except for the 2-inch (5 cm) area right around your navel (belly button)
  - Front of upper legs (thighs)
  - Back of upper arms (injection by caregiver or healthcare provider only)

- Do not inject LEROCHOL together with other injectable drugs at the same site.
- Do not select an area of the skin that is tender, bruised, red, or hard. Avoid areas with scars or stretch marks.
- Do not inject through clothing.
- Choose a different site each time you give yourself an injection. If you need to use the same injection site, make sure it is not the same spot on the site you used last time.

Figure L

Step 9. Clean the injection site.

1. Clean the skin of the injection site with an alcohol wipe (see Figure M).
  - Do not touch or blow on the injection site again before giving the injection. Let the skin dry before injecting.

Figure M

Injecting LEROCHOL

Step 10. Remove the needle cap.

1. Hold the barrel of the prefilled syringe with the needle facing away from you.
2. Firmly grip the needle cap and pull it straight off (see Figure N).
  - Do not twist the needle cap.
  - Do not touch the plunger rod as this may cause the prefilled syringe to release medicine prior to injection.
  - You may see a drop of liquid at the tip of the needle. This is normal.
  - Do not remove any air bubbles in the prefilled syringe.
3. Dispose of the needle cap right away in an FDA-cleared sharps disposal container (see Figure N).
  - Do not re-cap the prefilled syringe as you may stick yourself or damage the needle.

Figure N

Step 11. Pinch the skin and insert the needle.

1. Hold the barrel of the prefilled syringe in one hand between the thumb and index fingers.
2. Gently pinch a fold of skin at the injection site with one hand.
3. With a quick and dart-like motion, insert the needle completely into the pinched skin at a 45 to 90-degree angle (see Figure O).

Figure O

Step 12. Give the injection.

1. Hold the pinch.
2. Slowly push the plunger rod all the way down until the prefilled syringe is empty (see Figure P).

Figure P

Step 13. Remove the prefilled syringe.

1. When the prefilled syringe is empty, gently remove the needle from the injection site (see Figure Q).

Figure Q

Step 14. Care for the injection site.

1. If any bleeding happens, gently press a cotton ball or gauze on the injection site and hold for several seconds (see Figure R). Apply an adhesive bandage if needed.

Figure R

Storing LEROCHOL

- Store LEROCHOL in the refrigerator between 36°F to 46°F (2°C to 8°C) in the original carton until ready to use and to protect from light.
- If needed, LEROCHOL may be kept at room temperature between 68°F to 77°F (20°C to 25°C) in the original carton for up to 3 months after being removed from the refrigerator. Throw away LEROCHOL that has been stored at room temperature for more than 3 months.
- Do not freeze.
- Do not shake.

Keep LEROCHOL and all medicines out of reach of children.

Disposing of LEROCHOL

Step 15. Dispose of used syringe.

1. Put the used syringe in an FDA-cleared sharps disposal container right away after injection (see Figure S).
  - Do not re-cap the syringe as you may stick yourself.
  - Do not reuse the syringe.
  - Do not throw away your syringe in your household trash.
  - Do not recycle your used FDA-cleared sharps disposal container.

Figure S

If you do not have an FDA-cleared sharps disposal container, you may use a household container that is:

- made of heavy-duty plastic,
- can be closed with a tight-fitting, puncture-resistant lid without sharps being able to come out,
- upright and stable during use,
- leak-resistant, and
- properly labeled to warn of hazardous waste inside the container.

Disposing of sharps disposal containers:

When your sharps disposal container is almost full, you will need to follow your community guidelines for the right way to dispose of your FDA-cleared sharps disposal container.

There may be state or local laws about how you should throw away used needles and syringes.

Additional information about your FDA-cleared sharps disposal container.

For more information about safe sharps disposal, and for specific information about sharps disposal in the state that you live in, go to the FDA's website at:

http://www.fda.gov/safesharpsdisposal

Manufactured by: LIB Therapeutics, Inc., 5375 Medpace Way, Cincinnati, OH 45227-1543

Distributed by: LIB Therapeutics, Inc., 5375 Medpace Way, Cincinnati, OH 45227-1543

This Instructions for Use has been approved by the U.S. Food and Drug Administration.

Approved: December 2025, Version 0.3

PACKAGE LABEL

Principal Display Panel – 300 mg/1.2 mL Carton Label

NDC: 84685-300-01 Rx Only

LEROCHOL™
(lerodalcibep-liga)
Injection

300 mg/1.2 mL (250 mg/mL)

1 Single-dose Prefilled Syringe

300 mg/1.2 mL (250 mg/mL)
For Subcutaneous Injection
Single-dose Prefilled Syringe
Discard unused portion.
Sterile Solution – No Preservative

Keep out of the sight and reach of children

LIB
THERAPEUTICS

PACKAGE LABEL

Principal Display Panel – 300 mg/1.2 mL Tray Label

NDC: 84685-300-01

LEROCHOL™
(lerodalcibep-liga)
Injection

300 mg/1.2 mL (250 mg/mL)

Rx Only

1 Single-dose Prefilled Syringe

300 mg/1.2 mL (250 mg/mL)
For Subcutaneous Injection
Single-dose Prefilled Syringe
Discard unused portion.
Sterile Solution – No Preservative

PACKAGE LABEL

Principal Display Panel – 300 mg/1.2 mL Prefilled Syringe Label

NDC: 84685-300-01 Rx Only

LEROCHOL™
(lerodalcibep-liga)
Injection

300 mg/1.2 mL (250 mg/mL)

For Subcutaneous Injection
Single-dose Prefilled Syringe
Discard unused portion.
Sterile Solution – No Preservative